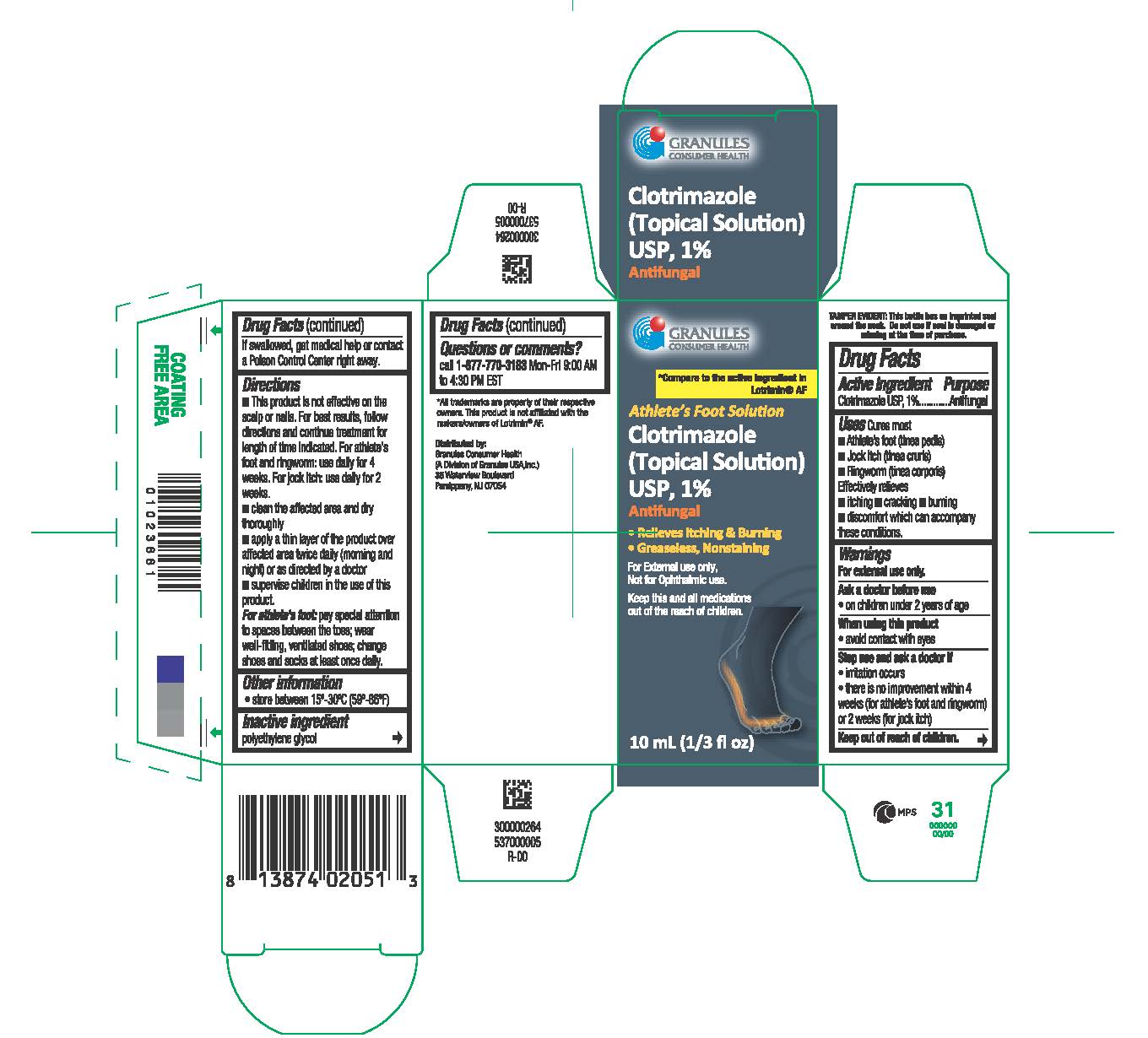 DRUG LABEL: Clotrimazole
NDC: 69848-001 | Form: SOLUTION
Manufacturer: Granules USA, Inc.
Category: otc | Type: HUMAN OTC DRUG LABEL
Date: 20251222

ACTIVE INGREDIENTS: CLOTRIMAZOLE 1 g/1 mL
INACTIVE INGREDIENTS: POLYETHYLENE GLYCOL 400

Athlete's Foot Solution
Clotrimazole
Topical solution, USP 1%

Active ingredient

Clotrimazole USP, 1%

Purpose

Antifungal

Uses

Cures most

- Athlete’s foot (tinea pedis),
- Jock itch (tinea cruris), and
- Ringworm (tinea corporis).

Effective relieves

• itching

• cracking

• burning

• discomfort which can accompany these conditions

Warning

For external use only

Ask a doctor before use

- on children under 2 years of age

When using this product

avoid contact with eyes

Stop use and ask a doctor if

- irritation occurs
- there is no improvement within 4 weeks (for athlete’s foot and ringworm) or 2 weeks (for jock itch)

Keep out of the reach of children.

If swallowed, get medical help or contact a Poison Control Center right away.

Directions

- this product is not effective on the scalp or nails. For best results, follow directions and continue treatment for length of time indicated. For athlete's foot and ringworm: use daily for 4 weeks. For jock itch: use daily for 2 weeks.
- clean the affected area and dry thoroughly
- apply a thin layer of the product over affected area twice daily (morning and night) or as directed by a doctor
- supervise children in the use of this product

For athlete's foot: pay special attention to spaces between the toes; wear well-fitting, ventilated shoes; change shoes and socks at least once daily

Other information

■ store between 15°-30°C (59°-86°F)

Inactive ingredient

polyethylene glycol 400.

Questions or comments?

call 1-877-770-3183 Mon-Fri 9:00 AM to 4:30 PM EST